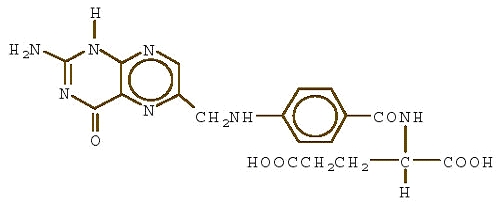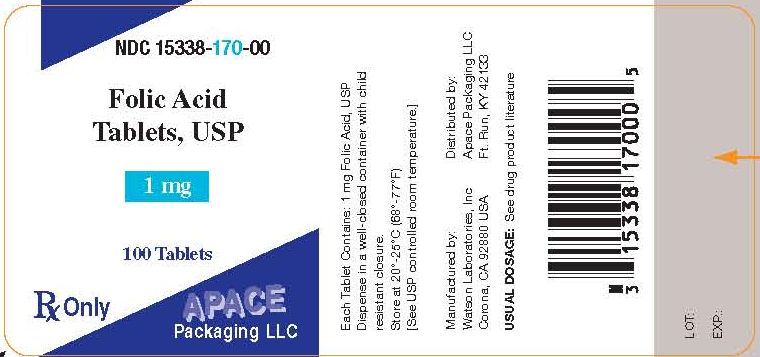 DRUG LABEL: Folic Acid
NDC: 15338-170 | Form: TABLET
Manufacturer: Apace Packaging
Category: prescription | Type: HUMAN PRESCRIPTION DRUG LABEL
Date: 20091228

ACTIVE INGREDIENTS: FOLIC ACID 1 mg/1 1
INACTIVE INGREDIENTS: LACTOSE MONOHYDRATE; CELLULOSE, MICROCRYSTALLINE; SODIUM STARCH GLYCOLATE TYPE A POTATO; STEARIC ACID

FOLIC ACID
TABLETS, USP

DESCRIPTION

Folic acid, N-[p-[[(2-amino-4-hydroxy-6-pteridinyl) methyl]-amino] benzoyl]-L-glutamic acid, is a B complex vitamin containing a pteridine moiety linked by a methylene bridge to para-aminobenzoic acid, which is joined by a peptide linkage to glutamic acid. Conjugates of folic acid are present in a wide variety of foods, particularly liver, kidneys, yeast, and leafy green vegetables. Commercially available folic acid is prepared synthetically. Folic acid occurs as a yellow or yellowish-orange crystalline powder and is very slightly soluble in water and insoluble in alcohol. Folic acid is readily soluble in dilute solutions of alkali hydroxides and carbonates, and solutions of the drug may be prepared with the aid of sodium hydroxide or sodium carbonate, thereby forming the soluble sodium salt of folic acid (sodium folate). Aqueous solutions of folic acid are heat sensitive and rapidly decompose in the presence of light and/or riboflavin; solutions should be stored in a cool place protected from light.
The structural formula of folic acid is as follows:

C19H19N7O6 M.W. 441.40

Each tablet, for oral administration, contains 1 mg folic acid.
Folic Acid Tablets USP 1 mg contain the following inactive ingredients: lactose monohydrate, microcrystalline cellulose, sodium starch glycolate and stearic acid.

CLINICAL PHARMACOLOGY

Folic acid acts on megaloblastic bone marrow to produce a normoblastic marrow.

In man, an exogenous source of folate is required for nucleoprotein synthesis and the maintenance of normal erythropoiesis. Folic acid is the precursor of tetrahydrofolic acid, which is involved as a cofactor for transformylation reactions in the biosynthesis of purines and thymidylates of nucleic acids. Impairment of thymidylate synthesis in patients with folic acid deficiency is thought to account for the defective deoxyribonucleic acid (DNA) synthesis that leads to megaloblast formation and megaloblastic and macrocytic anemias.

Folic acid is absorbed rapidly from the small intestine, primarily from the proximal portion. Naturally occurring conjugated folates are reduced enzymatically to folic acid in the gastrointestinal tract prior to absorption. Folic acid appears in the plasma approximately 15 to 30 minutes after an oral dose; peak levels are generally reached within 1 hour. After intravenous administration, the drug is rapidly cleared from the plasma. Cerebrospinal fluid levels of folic acid are several times greater than serum levels of the drug. Folic acid is metabolized in the liver to 7,8-dihydrofolic acid and eventually to 5,6,7,8-tetrahydrofolic acid with the aid of reduced diphosphopyridine nucleotide (DPNH) and folate reductases. Tetrahydrofolic acid is linked in the N5 or N10 positions with formyl, hydroxymethyl, methyl, or formimino groups. N5-formyltetrahydrofolic acid is leucovorin. Tetrahydrofolic acid derivatives are distributed to all body tissues but are stored primarily in the liver. Normal serum levels of total folate have been reported to be 5 to 15 ng/mL; normal cerebrospinal fluid levels are approximately 16 to 21 ng/mL. Normal erythrocyte folate levels have been reported to range from 175 to 316 ng/mL. In general, folate serum levels below 5 ng/mL indicate folate deficiency, and levels below 2 ng/mL usually result in megaloblastic anemia.

After a single oral dose of 100 µg of folic acid in a limited number of normal adults, only a trace amount of the drug appeared in the urine. An oral dose of 5 mg in 1 study and a dose of 40 µg/kg of body weight in another study resulted in approximately 50% of the dose appearing in the urine. After a single oral dose of 15 mg, up to 90% of the dose was recovered in the urine. A majority of the metabolic products appeared in the urine after 6 hours; excretion was generally complete within 24 hours. Small amounts of orally administered folic acid have also been recovered in the feces. Folic acid is also excreted in the milk of lactating mothers.

INDICATIONS AND USAGE

Folic acid is effective in the treatment of megaloblastic anemias due to a deficiency of folic acid (as may be seen in tropical or nontropical sprue) and in anemias of nutritional origin, pregnancy, infancy, or childhood.

CONTRAINDICATIONS

Folic acid is contraindicated in patients who have shown previous intolerance to the drug.

WARNINGS

Administration of folic acid alone is improper therapy for pernicious anemia and other megaloblastic anemias in which vitamin B12 is deficient.

PRECAUTIONS

General

Folic acid in doses above 0.1 mg daily may obscure pernicious anemia in that hematologic remission can occur while neurologic manifestations remain progressive.

There is a potential danger in administering folic acid to patients with undiagnosed anemia, since folic acid may obscure the diagnosis of pernicious anemia by alleviating the hematologic manifestations of the disease while allowing the neurologic complications to progress. This may result in severe nervous system damage before the correct diagnosis is made. Adequate doses of vitamin B12 may prevent, halt, or improve the neurologic changes caused by pernicious anemia.

Drug Interactions

There is evidence that the anticonvulsant action of phenytoin is antagonized by folic acid. A patient whose epilepsy is completely controlled by phenytoin may require increased doses to prevent convulsions if folic acid is given.

Folate deficiency may result from increased loss of folate, as in renal dialysis and/or interference with metabolism (e.g., folic acid antagonists such as methotrexate); the administration of anticonvulsants, such as diphenylhydantoin, primidone, and barbiturates; alcohol consumption and especially, alcoholic cirrhosis; and the administration of pyrimethamine and nitrofurantoin.

False low serum and red cell folate levels may occur if the patient has been taking antibiotics, such as tetracycline, which suppress the growth of Lactobacillus casei.

Carcinogenesis, Mutagenesis, Impairment of Fertility

Long-term studies in animals to evaluate carcinogenic potential and studies to evaluate the mutagenic potential or effect on fertility have not been conducted.

Pregnancy

Teratogenic Effects

Pregnancy Category A

Folic acid is usually indicated in the treatment of megaloblastic anemias of pregnancy. Folic acid requirements are markedly increased during pregnancy, and deficiency will result in fetal damage (see INDICATIONS AND USAGE).

Studies in pregnant women have not shown that folic acid increases the risk of fetal abnormalities if administered during pregnancy. If the drug is used during pregnancy, the possibility of fetal harm appears remote. Because studies cannot rule out the possibility of harm, however, folic acid should be used during pregnancy only if clearly needed.

Nursing Mothers

Folic acid is excreted in the milk of lactating mothers. During lactation, folic acid requirements are markedly increased; however, amounts present in human milk are adequate to fulfill infant requirements, although supplementation may be needed in low-birth-weight infants, in those who are breast-fed by mothers with folic acid deficiency (50 µg daily), or in those with infections or prolonged diarrhea.

ADVERSE REACTIONS

Allergic sensitization has been reported following both oral and parenteral administration of folic acid.

Folic acid is relatively nontoxic in man. Rare instances of allergic responses to folic acid preparations have been reported and have included erythema, skin rash, itching, general malaise, and respiratory difficulty due to bronchospasm. One patient experienced symptoms suggesting anaphylaxis following injection of the drug. Gastrointestinal side effects, including anorexia, nausea, abdominal distention, flatulence, and a bitter or bad taste, have been reported in patients receiving 15 mg folic acid daily for 1 month. Other side effects reported in patients receiving 15 mg daily include altered sleep patterns, difficulty in concentrating, irritability, overactivity, excitement, mental depression, confusion, and impaired judgment. Decreased vitamin B12 serum levels may occur in patients receiving prolonged folic acid therapy.

In an uncontrolled study, orally administered folic acid was reported to increase the incidence of seizures in some epileptic patients receiving Phenobarbital, primidone, or diphenylhydantoin. Another investigator reported decreased diphenylhydantoin serum levels in folate-deficient patients receiving diphenylhydantoin who were treated with 5 mg or 15 mg of folic acid daily.

OVERDOSAGE

Except during pregnancy and lactation, folic acid should not be given in therapeutic doses greater than 0.4 mg daily until pernicious anemia has been ruled out. Patients with pernicious anemia receiving more than 0.4 mg of folic acid daily who are inadequately treated with vitamin B12 may show reversion of the hematologic parameters to normal, but neurologic manifestations due to vitamin B12 deficiency will progress. Doses of folic acid exceeding the Recommended Dietary Allowance (RDA) should not be included in multivitamin preparations; if therapeutic amounts are necessary, folic acid should be given separately.

DOSAGE AND ADMINISTRATION

Oral administration is preferred. Although most patients with melabsorption cannot absorb food folates, they are able to absorb folic acid given orally. Parenteral administration is not advocated but may be necessary in some individuals (e.g., patients receiving parenteral or enteral alimentation). Doses greater than 0.1 mg should not be used unless anemia due to vitamin B12 deficiency has been ruled out or is being adequately treated with a cobalamin. Daily doses greater than 1 mg do not enhance the hematologic effect, and most of the excess is excreted unchanged in the urine.

The usual therapeutic dosage in adults and children (regardless of age) is up to 1 mg daily. Resistant cases may require larger doses. When clinical symptoms have subsided and the blood picture has become normal, a daily maintenance level should be used, i.e., 0.1 mg for infants and up to 0.3 mg for children under 4 years of age, 0.4 mg for adults and children 4 or more years of age, and 0.8 mg for pregnant and lactating women, but never less than 0.1 mg/day. Patients should be kept under close supervision and adjustment of the maintenance level made if relapse appears imminent.

In the presence of alcoholism, hemolytic anemia, anticonvulsant therapy, or chronic infection, the maintenance level may need to be increased.

HOW SUPPLIED

Folic Acid Tablets USP 1 mg are 10/32”, scored, round, yellow tablets imprinted DAN DAN and 5216 supplied in bottles of 100 and 1000.

Dispense in a well-closed container with child-resistant closure.
Store at 20°- 25°C (68°- 77°F).
[See USP controlled room temperature.]

Watson Laboratories, Inc.
Corona, CA 92880 USA

Packaged by:
APACE Packaging, LLC
Fountain Run, KY 42133

PRINCIPAL DISPLAY PANEL

NDC 15338-170-00

Folic Acid
Tablets, USP

1 mg

100 Tablets

Rx Only

Each Tablet Contains: 1 mg Folic Acid, USP

Dispense in a well-closed container with child resistant closure.

Store at 20°- 25°C (68°- 77°F).

[See USP controlled room temperature.]

USUAL DOSAGE: See drug product literature